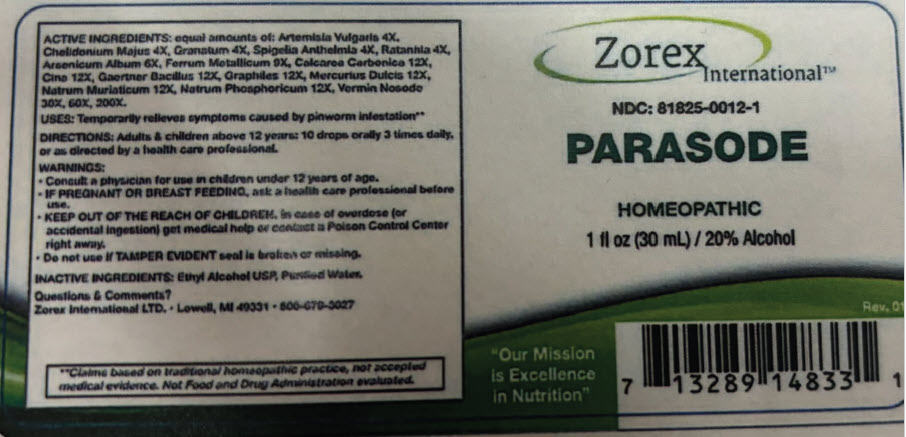 DRUG LABEL: Parasode
NDC: 81825-0012 | Form: LIQUID
Manufacturer: Zorex
Category: homeopathic | Type: HUMAN OTC DRUG LABEL
Date: 20250701

ACTIVE INGREDIENTS: artemisia vulgaris root 4 [hp_X]/1 mL; chelidonium majus whole 4 [hp_X]/1 mL; punica granatum root bark 4 [hp_X]/1 mL; spigelia anthelmia whole 4 [hp_X]/1 mL; krameria lappacea root 4 [hp_X]/1 mL; arsenic trioxide 6 [hp_X]/1 mL; iron 9 [hp_X]/1 mL; oyster shell calcium carbonate, crude 12 [hp_X]/1 mL; artemisia cina pre-flowering top 12 [hp_X]/1 mL; salmonella enterica enterica serovar enteritidis 12 [hp_X]/1 mL; graphite 12 [hp_X]/1 mL; calomel 12 [hp_X]/1 mL; sodium chloride 12 [hp_X]/1 mL; sodium phosphate, dibasic, heptahydrate 12 [hp_X]/1 mL
INACTIVE INGREDIENTS: Alcohol; Water

Parasode

Drug Facts

ACTIVE INGREDIENTS

equal amounts of: Artemisia Vulgaris 4X, Chelidonium Majus 4X, Granatum 4X, Spigelia Anthelmia 4X, Ratanhia 4X, Arsenicum Album 6X, Ferrum Metallicum 9X, Calcarea Carbonica 12X, Cina 12X, Gaertner Bacillus 12X, Graphites 12X, Mercurius Dulcis 12X, Natrum Muriaticum 12X, Natrum Phosphoricum 12X, Vermin Nosode 30X, 60X, 200X.

USES

PURPOSE

Temporarily relieves symptoms caused by pinworm infestation. [Claims based on traditional homeopathic practice, not accepted medical evidence. Not Food and Drug Administration evaluated.]

DIRECTIONS

Adults & children above 12 years: 10 drops orally 3 times daily, or as directed by a health care professional.

WARNINGS

PREGNANCY OR BREAST FEEDING

- Consult a physician for use in children under the age 12 years of age.
- IF PREGNANT OR BREAST-FEEDING, ask a health care professional before use.

KEEP OUT OF REACH OF CHILDREN

- KEEP OUT OF THE REACH OF CHILDREN. In case of overdose (or accidental ingestion) get medical help or contact Poison Control Center right away.

- Do not use if TAMPER EVIDENT seal is broken or missing.

INACTIVE INGREDIENTS

Ethyl Alcohol USP, Purified Water.

Questions & Comments?

Zorex International LTD. ∙ Lowell, MI 40331 ∙ 800-670-3027

PRINCIPAL DISPLAY PANEL - 30 mL Bottle Label

Zorex
International™

NDC: 81825-0012-1

PARASODE

HOMEOPATHIC

1 fl oz (30 mL) / 20% Alcohol

Rev. 01

"Our Mission
is Excellence
in Nutrition"